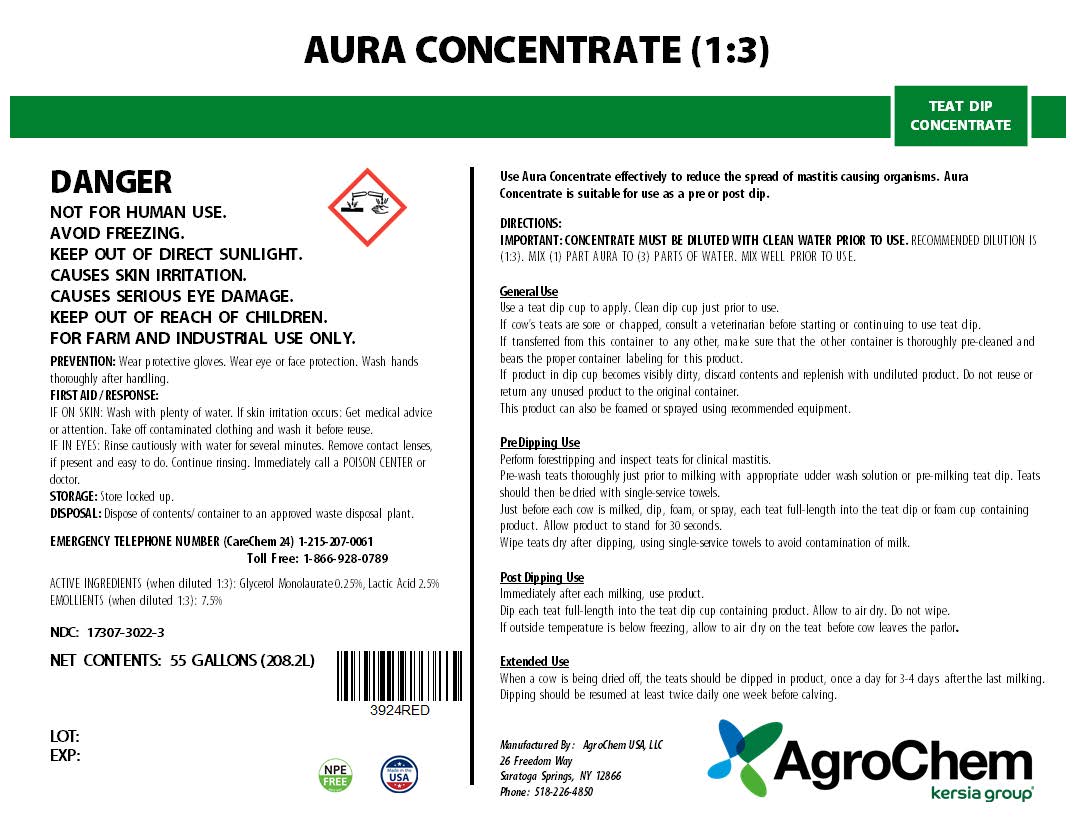 DRUG LABEL: Aura Concentrate
NDC: 17307-3022 | Form: SOLUTION
Manufacturer: AgroChem USA, LLC.
Category: animal | Type: OTC ANIMAL DRUG LABEL
Date: 20240717

ACTIVE INGREDIENTS: GLYCERYL LAURATE 0.01 kg/1 kg; LACTIC ACID 0.12 kg/1 kg
INACTIVE INGREDIENTS: SODIUM XYLENESULFONATE

Aura Concentrate

AURA CONCENTRATE

TEAT DIP CONCENTRATE

WARNINGS

DANGER

KEEP OUT OF REACH OF CHILDREN

WARNINGS AND PRECAUTIONS

NOT FOR HUMAN USE.

AVOID FREEZING.

KEEP OUT OF DIRECT SUNLIGHT.

CAUSES SKIN IRRITATION.

CAUSES SERIOUS EYE DAMAGE.

FOR FARM AND INDUSTRIAL USE ONLY

PREVENTION: Wear protective gloves. Wear eye or face protection. Wash hands thoroughly after handling.

FIRST AID / RESPONSE:

IF ON SKIN: Wash with plenty of water. If skin irritation occurs: Get medical advice or attention. Take off contaminated clothing and wash it before reuse.

IF IN EYES: Rinse cautiously with water for several minutes. Remove contact lenses, if present and easy to do. Continue rinsing. Immediately call a POISON CENTER or doctor.

STORAGE: Store locked up.

DISPOSAL: Dispose of contents/ container to an approved waste disposal plan

EMERGENCY TELEPHONE NUMBER (CareChem 24) 1-215-207-0061 Toll Free: 1-866-928-0789

ACTIVE INGREDIENT

ACTIVE INGREDIENTS (when diluted 1:3): Glycerol Monolaurate 0.25%, Lactic Acid 2.5%

INACTIVE INGREDIENT

EMOLLIENTS (when diluted 1:3): 7.5%

NDC: 17307-3022-3

NET CONTENTS: 55 GALLON (208.2L)

Use Aura Concentrate effectively to reduce the spread of mastitis causing organisms. Aura Concentrate is suitable for use as a pre or post dip.

DIRECTIONS:

IMPORTANT: CONCENTRATE MUST BE DILUTED WITH CLEAN WATER PRIOR TO USE. RECOMMENDED DILUTION IS (1:3). MIX (1) PART AURA TO (3) PARTS OF WATER. MIX WELL PRIOR TO USE.

General Use

Use a teat dip cup to apply. Clean dip cup just prior to use.

If cow’s teats are sore or chapped, consult a veterinarian before starting or continuing to use teat dip.

If transferred from this container to any other, make sure that the other container is thoroughly pre-cleaned and bears the proper container labeling for this product.

If product in dip cup becomes visibly dirty, discard contents and replenish with undiluted product. Do not reuse or return any unused product to the original container.

This product can also be foamed or sprayed using recommended equipment.

Pre Dipping Use

Perform forestripping and inspect teats for clinical mastitis.

Pre-wash teats thoroughly just prior to milking with appropriate udder wash solution or pre-milking teat dip. Teats should then be dried with single-service towels.

Just before each cow is milked, dip, foam, or spray, each teat full-length into the teat dip or foam cup containing product. Allow product to stand for 30 seconds.

Wipe teats dry after dipping, using single-service towels to avoid contamination of milk.

Post Dipping Use

Immediately after each milking, use product.

Dip each teat full-length into the teat dip cup containing product. Allow to air dry. Do not wipe.

If outside temperature is below freezing, allow to air dry on the teat before cow leaves the parlor.

Extended Use

When a cow is being dried off, the teats should be dipped in product, once a day for 3-4 days after the last milking. Dipping should be resumed at least twice daily one week before calving.

Manufactured By:

AgroChem USA, LLC 26 Freedom Way • Saratoga Springs, NY 12866 • (518)226-4850